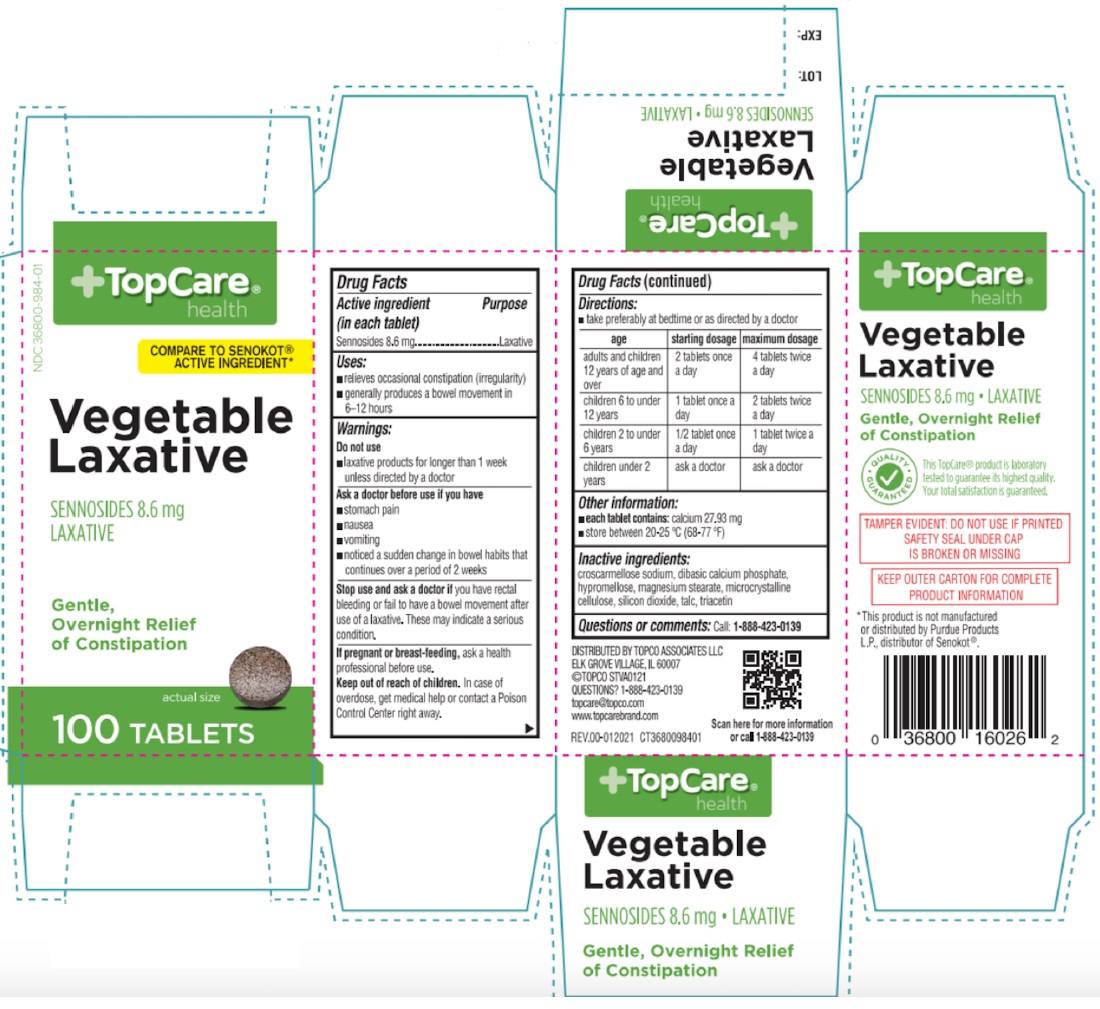 DRUG LABEL: Laxative Senna
NDC: 36800-984 | Form: TABLET, COATED
Manufacturer: TOPCO ASSOCIATES LLC
Category: otc | Type: HUMAN OTC DRUG LABEL
Date: 20250101

ACTIVE INGREDIENTS: SENNOSIDES 8.6 mg/1 1
INACTIVE INGREDIENTS: CROSCARMELLOSE SODIUM; ANHYDROUS DIBASIC CALCIUM PHOSPHATE; HYPROMELLOSE, UNSPECIFIED; MAGNESIUM STEARATE; MICROCRYSTALLINE CELLULOSE; SILICON DIOXIDE; TALC; TRIACETIN

Laxative Senna

Active ingredient (in each tablet)

Sennosides 8.6 mg

Purpose

Laxative

Uses:

• relieves occasional constipation (irregularity)
• generally produces a bowel movement in 6-12 hours

Warnings:

Do not use
• laxative products for longer than 1 week unless directed by a doctor

Ask a doctor before use if you have
• stomach pain
• nausea
• vomiting
• noticed a sudden change in bowel habits that continues over a period of 2 weeks

Stop use and ask a doctor if you have rectal bleeding or fail to have a bowel movement after use of a laxative. These may indicate a serious condition,

If pregnant or breast-feeding, ask a health professional before use.

Keep out of reach of children. In case of overdose, get medical help or contact a Poison Control Center right away.

Directions:

• take preferably at bedtime or as directed by a doctor

age | starting dosage | maximum dosage
adults and children 12 years of age and over | 2 tablets once a day | 4 tablets twice a day
children 6 to under 12 years | 1 tablet once a day | 2 tablets twice a day
children 2 to under 6 years | 1/2 tablet once a day | 1 tablet twice a day
children under 2 years | ask a doctor | ask a doctor

Other information:

• each tablet contains: calcium 27.93 mg
• store between 20-25 °C (68-77 °F)

Inactive ingredients:

croscarmellose sodium, dibasic calcium phosphate, hypromellose, magnesium stearate, microcrystalline cellulose, silicon dioxide, talc, triacetin

Questions or comments:

Call: 1-888-423-0139

+TopCare® health

COMPARE TO SENOKOT® ACTIVE INGREDIENT*

Vegetable Laxative

Gentle, Overnight Relief of Constipation

DISTRIBUTED BY TOPCO ASSOCIATES LLC
ELK GROVE VILLAGE, IL 60007

©TOPCO STVA0121

topcare@topco.com

www.topcarebrand.com

This TopCare® product is laboratory tested to guarantee its highest quality. Your total satisfaction is guaranteed.

TAMPER EVIDENT: DO NOT USE IF PRINTED SAFETY SEAL UNDER CAP IS BROKEN OR MISSING

KEEP OUTER CARTON FOR COMPLETE PRODUCT INFORMATION

*This product is not manufactured or distributed by Purdue Products L.P., distributor of Senokot®.